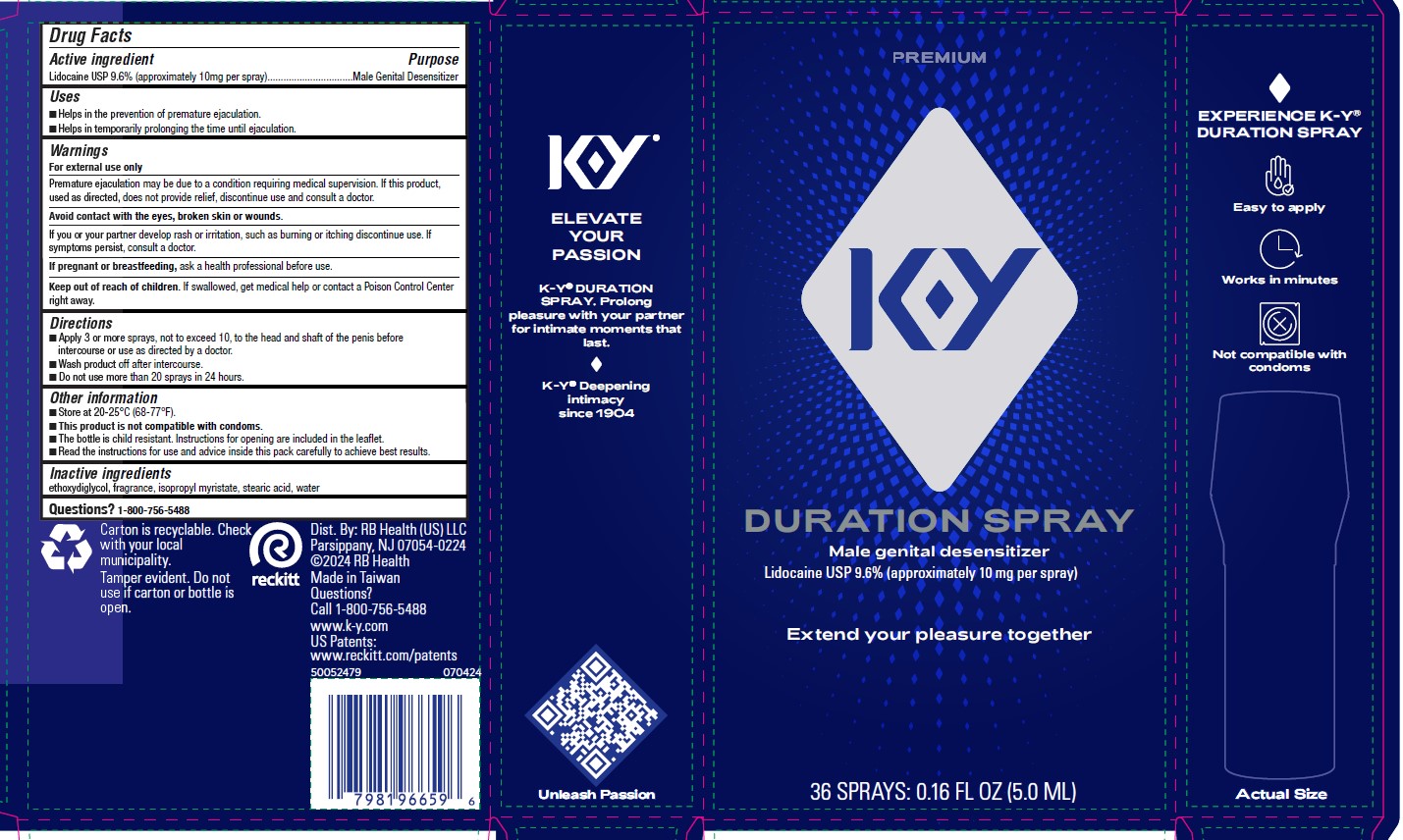 DRUG LABEL: KY
NDC: 72854-682 | Form: SPRAY, METERED
Manufacturer: RB Health (US) LLC
Category: otc | Type: HUMAN OTC DRUG LABEL
Date: 20250213

ACTIVE INGREDIENTS: LIDOCAINE 96 mg/1 mL
INACTIVE INGREDIENTS: DIETHYLENE GLYCOL MONOETHYL ETHER; ISOPROPYL MYRISTATE; STEARIC ACID; WATER

KY®
Duration®Spray

Drug Facts

Active ingredient

Lidocaine USP 9.6% (approximately 10mg per spray)

Purpose

Male Genital Desensitizer

Uses

- Helps in the prevention of premature ejaculation
- Helps in temporarily prolonging the time until ejaculation

Warnings

For external use only

Premature ejaculation may be due to a condition requiring medical supervision. If this product, used as directed, does not provide relief, discontinue use and consult a doctor.

Avoid contact with the eyes

If you or your partner develop rash or irritation, such as burning or itching discontinue use. If symptoms persist, consult a doctor.

PREGNANCY OR BREAST FEEDING

If pregnant or breastfeeding,ask a health professional before use

Keep out of reach of children.If swallowed, get medical help or contact a Poison Control Center right away.

Directions

- Apply 3 or more sprays, not to exceed 10, to the head and shaft of the penis before intercourse, or use as directed by a doctor
- Wash product off after intercourse
- Do not use more than 20 sprays in 24 hours

Other information

- Storage instructions: Store at 20-25°C (68-77°F).
- This product is not compatible with condoms.
- The bottle is child resistant. Instructions for opening are included in the leaflet.
- Read the instructions for use and advice inside this pack carefully to achieve best results.

Inactive ingredients

ethoxydiglycol, fragrance, isopropyl myristate, stearic acid

Questions?

1-800-756-5488

Distributed by:RB Health (US), Parsippany, NJ 07054-0224

Made in Taiwan

PRINCIPAL DISPLAY PANEL - 5.0 mL Bottle Carton

36
sprays

KY®
EST
1904

duration®

spray for him

male genital desensitizer
Lidocaine USP 9.6% (approximately 10mg per spray)

36 Sprays 0.16 fl oz (5.0 mL)